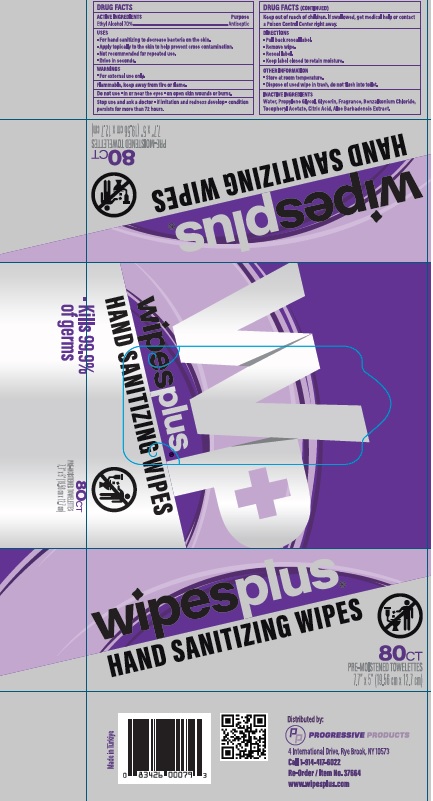 DRUG LABEL: Ethyl Alcohol
NDC: 67151-707 | Form: SWAB
Manufacturer: PROGRESSIVE PRODUCTS, LLC
Category: otc | Type: HUMAN OTC DRUG LABEL
Date: 20221014

ACTIVE INGREDIENTS: ALCOHOL 0.7 mL/1 1
INACTIVE INGREDIENTS: PROPYLENE GLYCOL; BENZALKONIUM CHLORIDE; CITRIC ACID MONOHYDRATE; GLYCERIN; .ALPHA.-TOCOPHEROL ACETATE; ALOE VERA LEAF; WATER

DRUG FACTS

Active ingredients

Ethyl Alcohol 70%

Purpose

Antiseptic

Uses

- For hand sanitizing to decrease bacteria on the skin.
- Apply topically to the skin to help prevent cross contamination.
- Not recommended for repeated use.
- Dries in seconds

Warnings

- For external use only.

Flammable

keep away from fire or flame.

Do not use

- in or near the eyes
- on open skin wounds or burns.

Stop use and ask a doctor

- if irritation and redness develop
- condition persists for more than 72 hours.

Keep out of reach of children.

If swallowed, get medical help or contact a Poison Control Center right away.

Directions

- Pull back reseal label.
- Remover wipe.
- Reseal label
- Keep label closed to retain moisture.

Other Information

- Store at room temperature.
- Dispose of used wipe in trash, do not flush into toilet.

Inactive Ingredients

Water, Propylene Glycol, Glycerin, Fragrance, Benzalkonium Chloride, Tocopheryl Acetate, Citric Acid, Aloe Barbadensis Extract.

Principal Display Panel

Wipesplus

SANITIZING WIPES

80CT

PRE-MOISTENED TOWELETTES